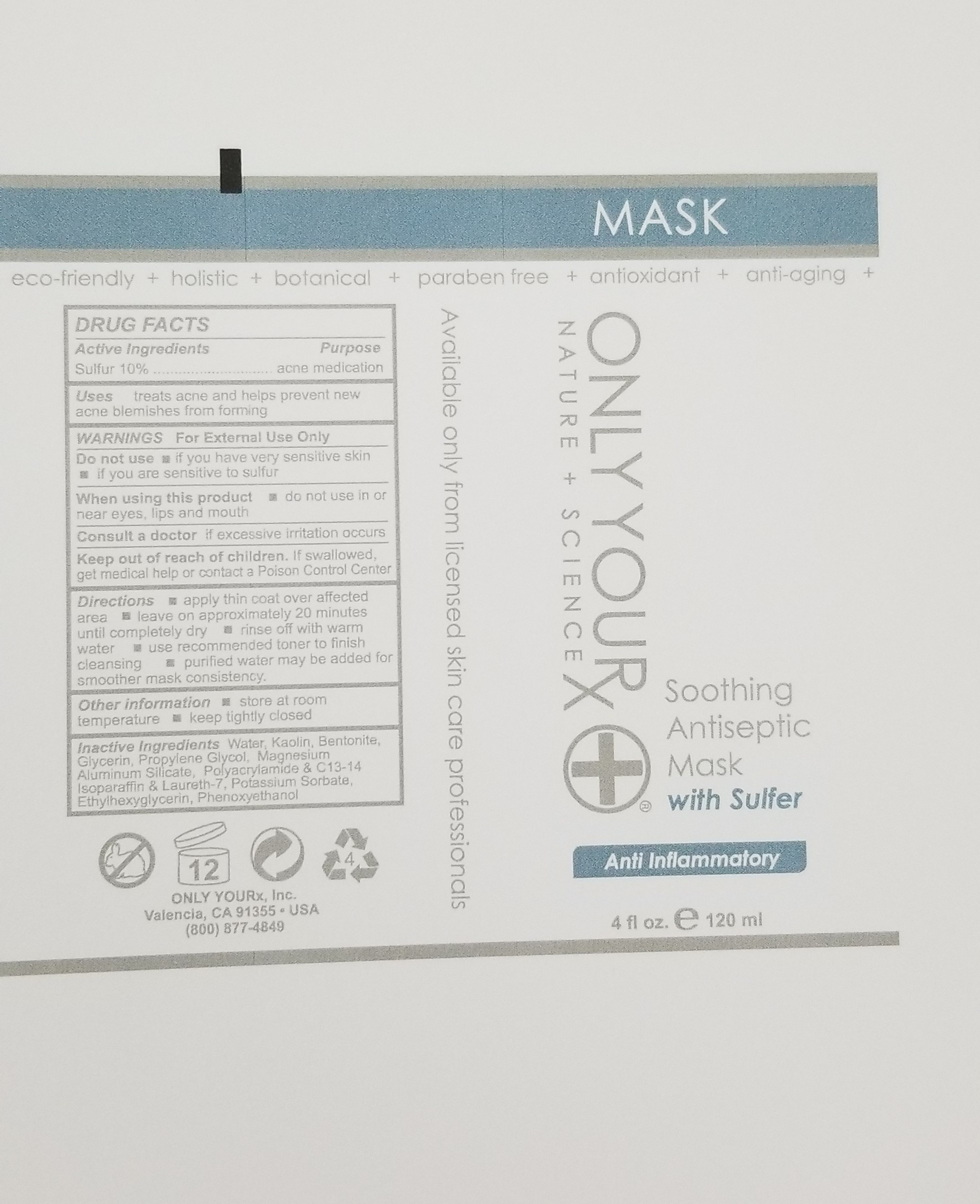 DRUG LABEL: Soothing Antiseptic Mask with Sulfur
NDC: 70367-010 | Form: CREAM
Manufacturer: Only Yourx, Inc.
Category: otc | Type: HUMAN OTC DRUG LABEL
Date: 20200123

ACTIVE INGREDIENTS: SULFUR 10 g/100 mL
INACTIVE INGREDIENTS: PHENOXYETHANOL; POLYACRYLAMIDE (10000 MW); WATER; KAOLIN; BENTONITE; GLYCERIN; 2-(1-CHLOROCYCLOPROPYL)-3-(2-CHLOROPHENYL)-1,2-PROPANEDIOL; MAGNESIUM ALUMINUM SILICATE; C13-14 ISOPARAFFIN; LAURETH-7; POTASSIUM SORBATE; ETHYLHEXYLGLYCERIN

Active Ingredients: Sulfur 10%

INACTIVE INGREDIENT

Inactive Ingredients: Water, Kaolin, Bentonite, Glycerin, Propylene Glycol, Magnesium Aluminum Silicate, Polyacrylamide, C13-14 Isoparaffin, Laureth-7, Potassium Sorbate, Ethyl hexylglycerin, Phenoxyethanol

DOSAGE AND ADMINISTRATION

Directions: apply thin coat over affe3cted area; leave on approximately 20 minutes until completely dry; rinse off with warm watre; use recommended toner to finish cleansing; purified water may be added for smoothr mask consistency

INDICATIONS AND USAGE

Uses: treats acne and helps prevent new acne blemishes from forming

PURPOSE

acne mediaction; to treat and prevent acne

Warnings: For External Use Only

When using this product: do not use in or near eyes, lips, and mouth

Consult a doctor: if excessive irritation occurs

Other information: store at room temperature; keep tightly closed

Keep out of reach of children. If swallowed, get medical help or contact a Poison Control Center.